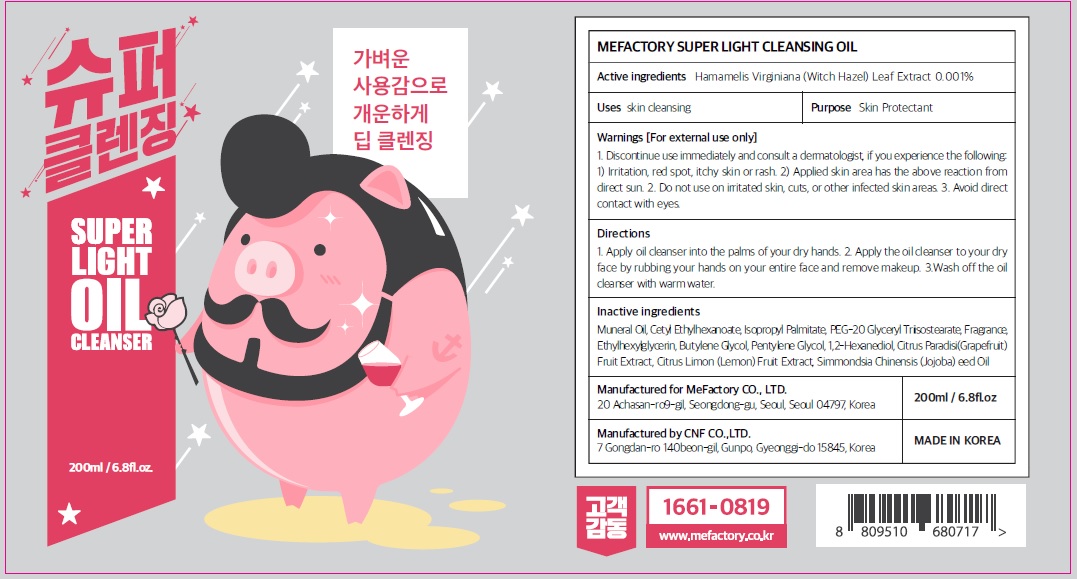 DRUG LABEL: Mefactory Super Light Cleansing
NDC: 70908-180 | Form: OIL
Manufacturer: MeFactory Co., Ltd.
Category: otc | Type: HUMAN OTC DRUG LABEL
Date: 20171229

ACTIVE INGREDIENTS: Witch Hazel 0.002 g/200 mL
INACTIVE INGREDIENTS: Mineral Oil; Cetyl Ethylhexanoate

ACTIVE INGREDIENT

Active ingredients: Hamamelis Virginiana (Witch Hazel) Leaf Extract 0.001%

INACTIVE INGREDIENT

Inactive ingredients: Mineral Oil, Cetyl Ethylhexanoate, Isopropyl Palmitate, PEG-20 Glyceryl Triisostearate, Fragrance, Ethylhexylglycerin, Butylene Glycol, Pentylene Glycol, 1,2-Hexanediol, Citrus Paradisi (Grapefruit) Fruit Extract, Citrus Limon (Lemon) Fruit Extract, Simmondsia Chinensis (Jojoba) Seed Oil

PURPOSE

Purpose: Skin Protectant

WARNINGS

Warnings: For external use only 1. Discontinue use immediately and consult a dermatologist, if you experience the following: 1) Irritation, red spot, itchy skin or rash 2) Applied skin area has the above reaction from direct sun. 2. Do not use on irritated skin, cuts, or other infected skin areas. 3. Avoid direct contact with eyes

KEEP OUT OF REACH OF CHILDREN

Uses

Uses: Skin cleansing

Directions

Directions: 1. Apply oil cleanser into the palms of your dry hands 2. Apply the oil cleanser to your dry face by rubbing your hands on your entire face and remove makeup 3.Wash off the oil cleanser with warm water